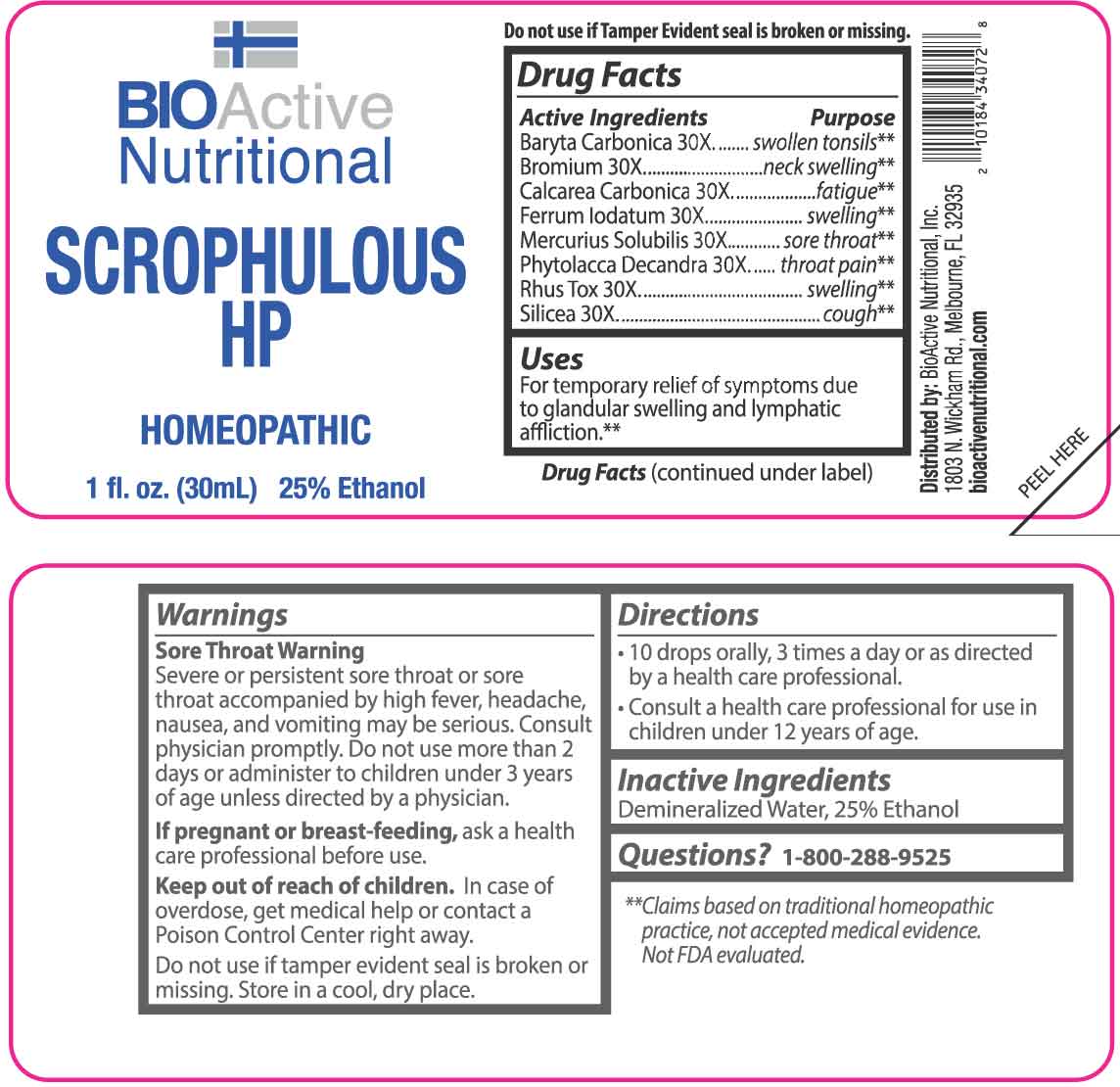 DRUG LABEL: SCROPHULOUS
NDC: 43857-0267 | Form: LIQUID
Manufacturer: BioActive Nutritional, Inc.
Category: homeopathic | Type: HUMAN OTC DRUG LABEL
Date: 20251218

ACTIVE INGREDIENTS: BARIUM CARBONATE 30 [hp_X]/1 mL; BROMINE 30 [hp_X]/1 mL; OYSTER SHELL CALCIUM CARBONATE, CRUDE 30 [hp_X]/1 mL; FERROUS IODIDE 30 [hp_X]/1 mL; MERCURIUS SOLUBILIS 30 [hp_X]/1 mL; PHYTOLACCA AMERICANA ROOT 30 [hp_X]/1 mL; TOXICODENDRON PUBESCENS LEAF 30 [hp_X]/1 mL; SILICON DIOXIDE 30 [hp_X]/1 mL
INACTIVE INGREDIENTS: WATER; ALCOHOL

DRUG FACTS:

ACTIVE INGREDIENTS:

Baryta Carbonica 30X, Bromium 30X, Calcarea Carbonica 30X, Ferrum Iodatum 30X, Mercurius Solubilis 30X, Phytolacca Decandra 30X, Rhus Tox 30X, Silicea 30X.

PURPOSE:

Baryta Carbonica - Swollen tonsils,** Bromium - neck swelling,** Calcarea Carbonica - fatigue,** Ferrum Iodatum - swelling,** Mercurius Solubilis - sore throat,** Phytolacca Decandra - throat pain,** Rhus Tox - swelling,** Silicea - cough**

**Claims based on traditional homeopathic practice, not accepted medical evidence. Not FDA evaluated.

USES:

For temporary relief of symptoms due to glandular swelling and lymphatic affliction.**

**Claims based on traditional homeopathic practice, not accepted medical evidence. Not FDA evaluated.

WARNINGS:

Sore Throat Warning

Severe or persistent sore throat or sore throat accompanied by high fever, headache, nausea, and vomiting may be serious. Consult physician promptly. Do not use more than 2 days or administer to children under 3 years of age unless directed by a physician.

If pregnant or breast-feeding, ask a health care professional before use.

Keep out of reach of children. In case of overdose, get medical help or contact a Poison Control Center right away.

Do not use if tamper evident seal is broken or missing.

Store in a cool, dry place.

KEEP OUT OF REACH OF CHILDREN

In case of overdose, get medical help or contact a Poison Control Center right away.

DIRECTIONS:

• 10 drops orally, 3 times a day or as directed by a health care professional.

• Consult a health care professional for use in children under 12 years of age.

INACTIVE INGREDIENTS:

Demineralized Water, 25% Ethanol

QUESTIONS:

Distributed by:
BioActive Nutritional, Inc.
1803 N. Wickham Rd.
Melbourne, FL 32935
bioactivenutritional.com

1-800-288-9525

PACKAGE LABEL DISPLAY:

BIOActive Nutritional

SCROPHULOUS HP

HOMEOPATHIC

1 fl. oz. (30 mL)